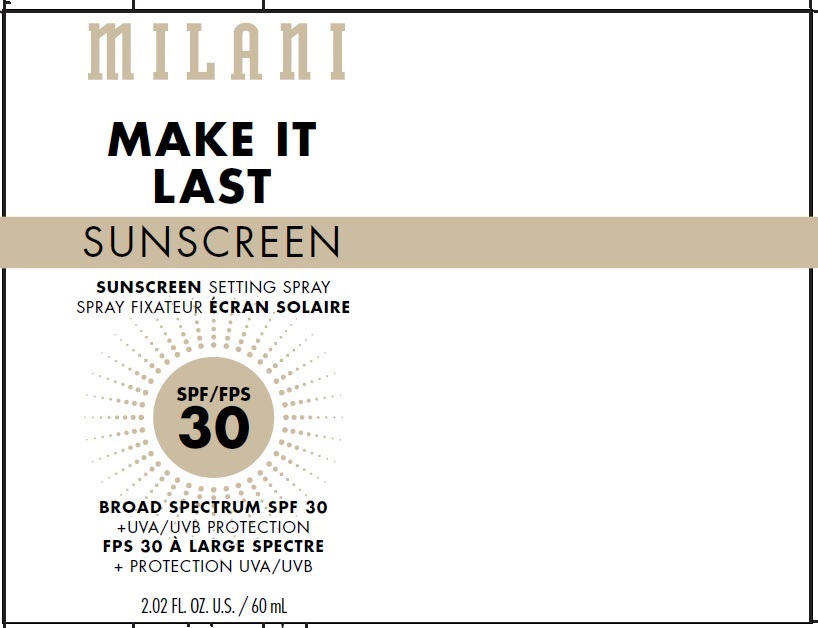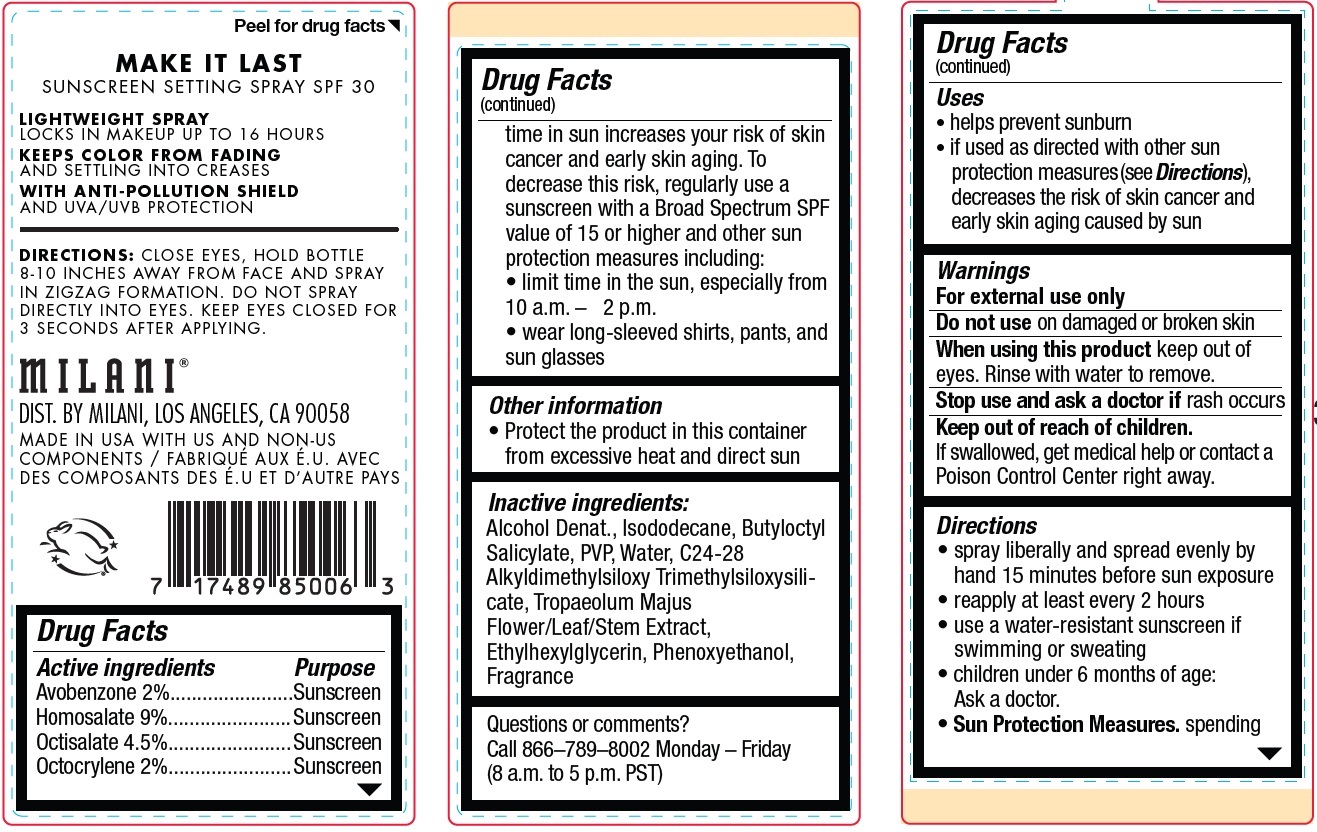 DRUG LABEL: MILANI MAKE IT LAST SUNSCREEN SETTING SPF 30
NDC: 68577-040 | Form: LIQUID
Manufacturer: Cosmax Usa, Corporation
Category: otc | Type: HUMAN OTC DRUG LABEL
Date: 20241226

ACTIVE INGREDIENTS: AVOBENZONE 20 mg/1 mL; HOMOSALATE 90 mg/1 mL; OCTISALATE 45 mg/1 mL; OCTOCRYLENE 20 mg/1 mL
INACTIVE INGREDIENTS: ALCOHOL; ISODODECANE; BUTYLOCTYL SALICYLATE; POVIDONE, UNSPECIFIED; WATER; TROPAEOLUM MAJUS FLOWERING TOP; ETHYLHEXYLGLYCERIN; PHENOXYETHANOL

MILANI MAKE IT LAST SUNSCREEN SETTING SPRAY SPF 30

Active ingredients

Avobenzone 2%

Homosalate 9%

Octisalate 4.5%

Octocrylene 2%

Purpose

Sunscreen

Uses

• helps prevent sunburn
• if used as directed with other sun protection measures (see Directions), decreases the risk of skin cancer and early skin aging caused by sun

Warnings

For external use only

Do not use

on damaged or broken skin

When using this product

keep out of eyes. Rinse with water to remove.

Stop use and ask a doctor if

rash occurs

Keep out of reach of children.

If swallowed, get medical help or contact a Poison Control Center right away.

Directions

• spray liberally and spread evenly by hand 15 minutes before sun exposure
• reapply at least every 2 hours
• use a water-resistant sunscreen if swimming or sweating
• children under 6 months of age: Ask a doctor.
• Sun Protection Measures.spending time in sun increases your risk of skin cancer and early skin aging. To decrease this risk, regularly use a sunscreen with a Broad Spectrum SPF value of 15 or higher and other sun protection measures including:
• limit time in the sun, especially from 10 a.m. – 2 p.m.
• wear long-sleeved shirts, pants, and sun glasses

Other information

- Protect the product in this container from excessive heat and direct sun

Inactive ingredients:

Alcohol Denat., Isododecane, Butyloctyl Salicylate, PVP, Water, C24-28 Alkyldimethylsiloxy Trimethylsiloxysilicate, Tropaeolum Majus Flower/Leaf/Stem Extract, Ethylhexylglycerin, Phenoxyethanol, Fragrance

Questions or comments?

Call 866–789–8002 Monday – Friday (8 a.m. to 5 p.m. PST)